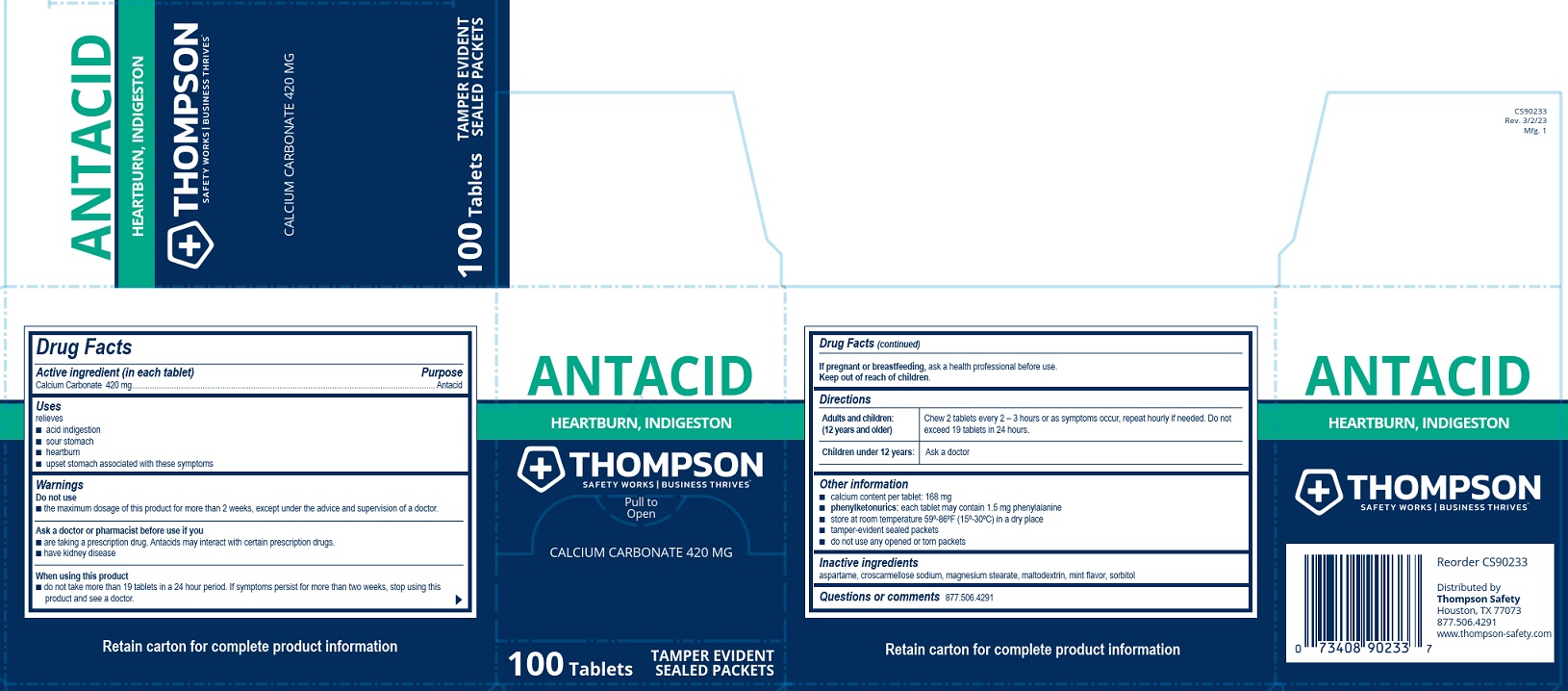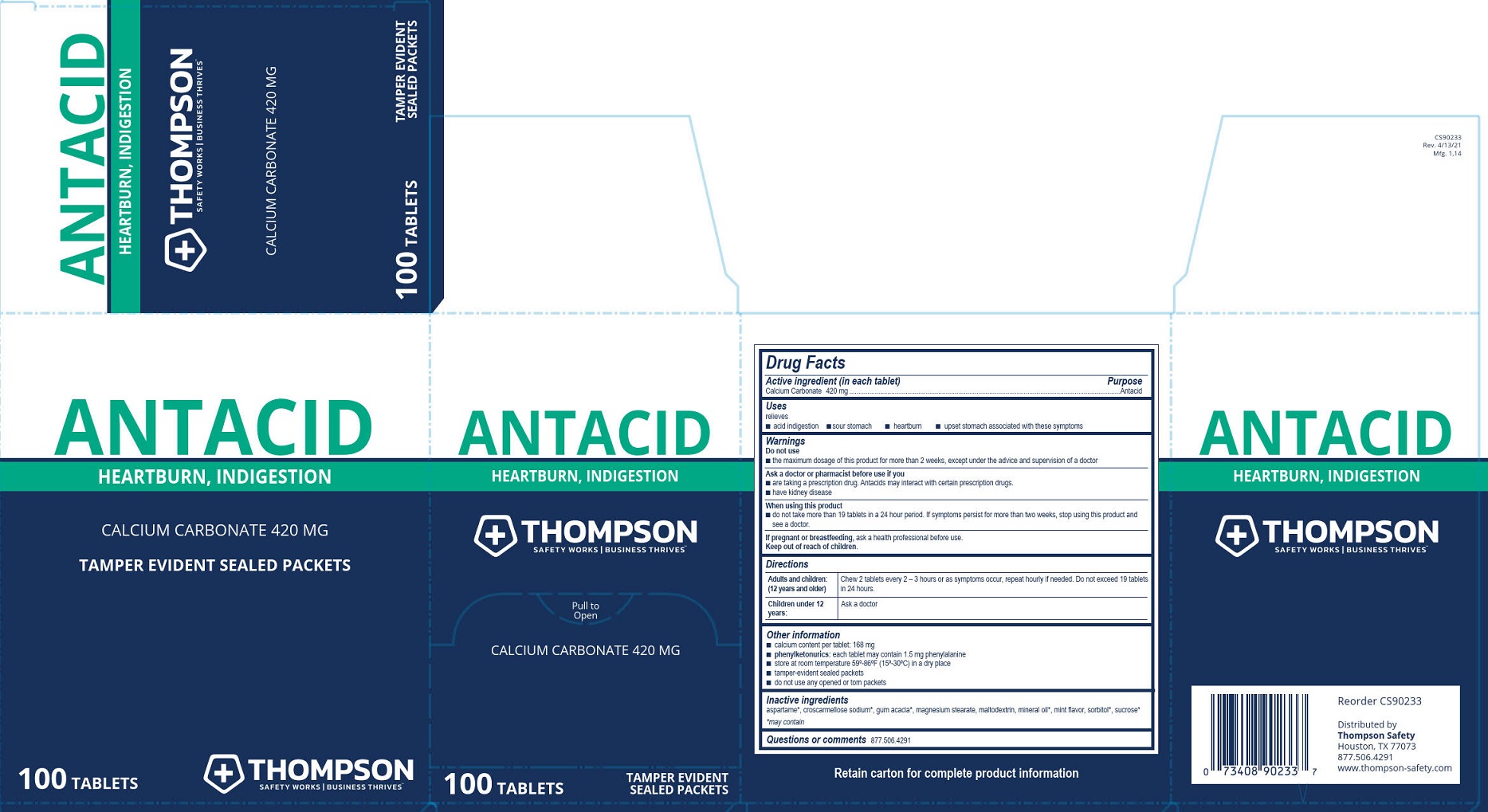 DRUG LABEL: Thompson Antacid
NDC: 73408-921 | Form: TABLET, CHEWABLE
Manufacturer: Thompson
Category: otc | Type: HUMAN OTC DRUG LABEL
Date: 20250908

ACTIVE INGREDIENTS: CALCIUM CARBONATE 420 mg/1 1
INACTIVE INGREDIENTS: MINERAL OIL; SORBITOL; ASPARTAME; CROSCARMELLOSE SODIUM; MAGNESIUM STEARATE; MALTODEXTRIN

Thompson Antacid

Drug Facts

Active ingredient (in each tablet)

Calcium Carbonate 420 mg

Purpose

Antacid

Uses

relieves

- acid indigestion
- sour stomach
- heartburn
- upset stomach associated with these symptoms

Warnings

Do not use

- the maximum dosage of this product for more than 2 weeks except under the advice and supervision of a doctor

Ask a doctor or pharmacists before use if you are

- are taking a prescription drug. Antacids may interact with certain prescription drugs.
- have kidney disease

When using this product

- do not take more than 19 tablets in a 24 hour period. If symptoms persist for more than 2 weeks, stop using this product and see a doctor.

PREGNANCY OR BREAST FEEDING

If pregnant or breast feeding, ask a health professional before use.

Keep out of the reach of children.

Directions

Adults and children: (12 years and older) Chew 2 tablets every 2 - 3 hours as symptoms occur, repeat hourly if needed. Do not exceed 19 tablets in 24 hours.

Children under 12 years: Ask a doctor

Other information

- calcium content per tablet: 168 mg
- phenylketonurics: each tablet may contain 1.5 mg phenylalanine
- store at room temperature 59-86°F (15-30°C) in a dry place
- tamper-evident sealed packets
- do not use any opened or torn packets

Inactive ingredients

aspartame, croscarmellose sodium, magnesium stearate, maltodextrin, mineral oil, mint flavor, sorbitol

Questions or comments? 877.506.4291

PACKAGE LABEL

Antacid

Thompson

Safety Works | Business Thrives™

Heartburn, Indigestion

Pull to Open

Calcium Carbonate 420 mg

100 Tablets

Tamper Evident

Sealed Packets